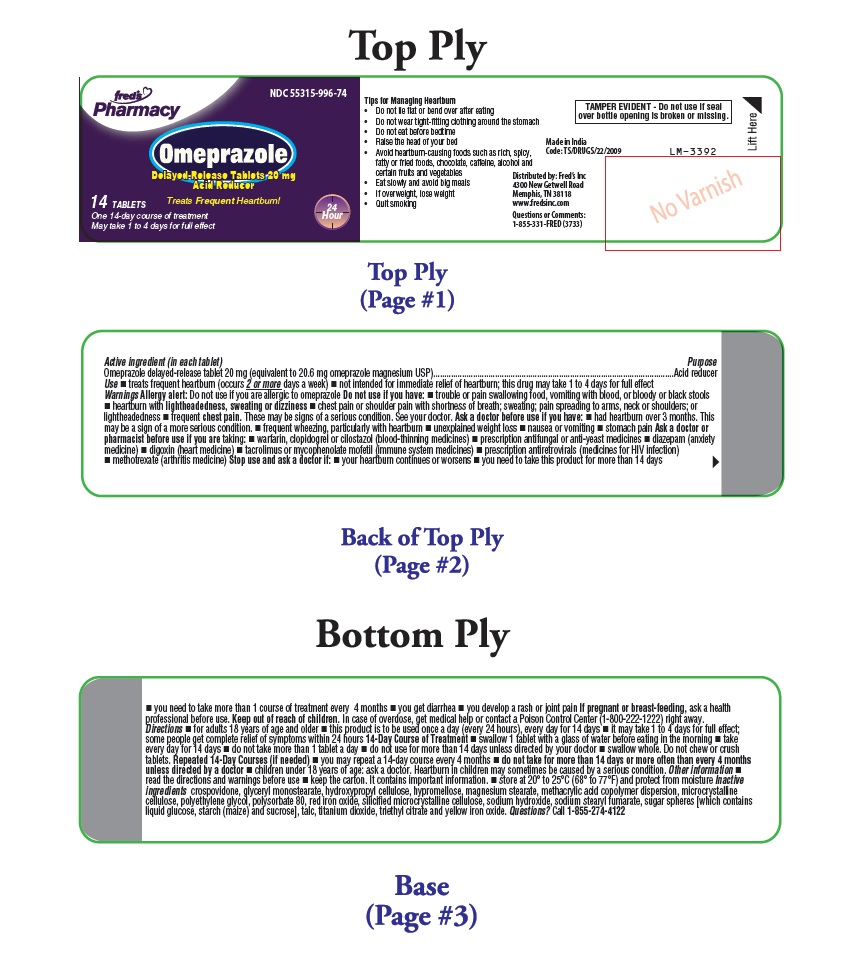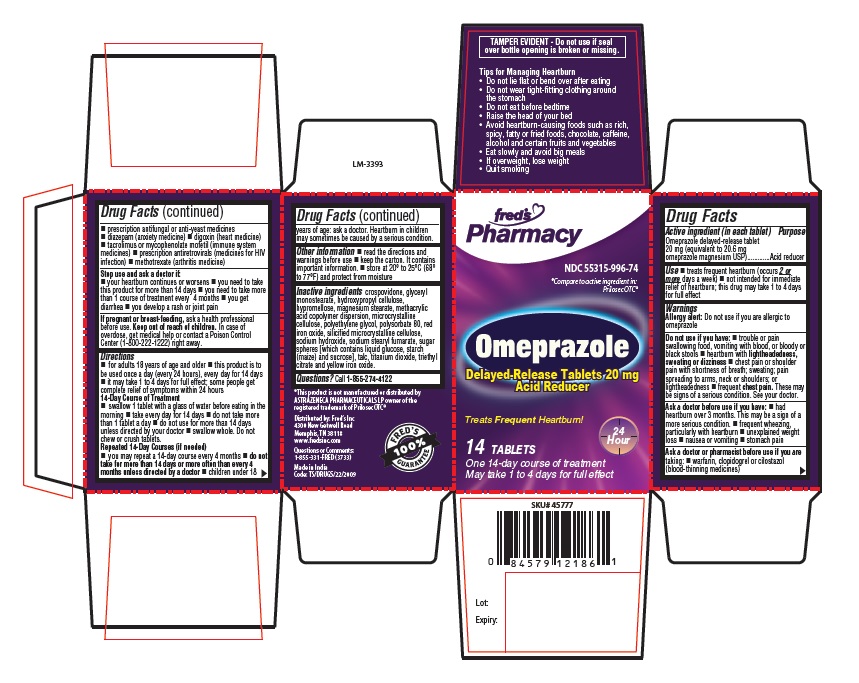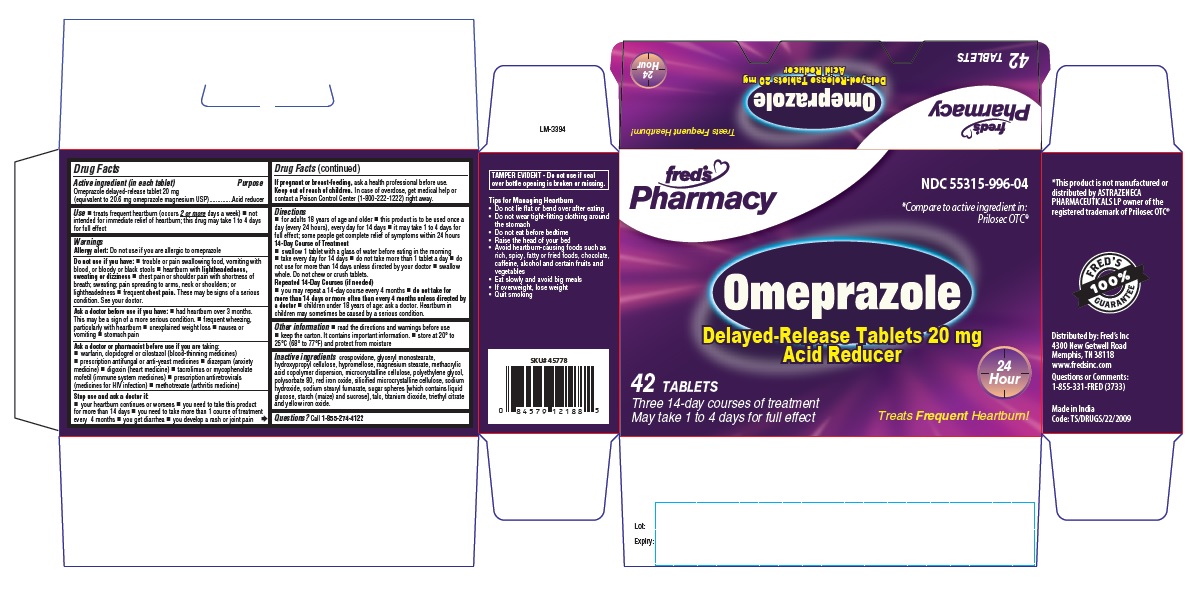 DRUG LABEL: Acid Reducer
NDC: 55315-996 | Form: TABLET, DELAYED RELEASE
Manufacturer: Fred's, Inc.
Category: otc | Type: Human OTC Drug Label
Date: 20240627

ACTIVE INGREDIENTS: OMEPRAZOLE MAGNESIUM 20 mg/1 1
INACTIVE INGREDIENTS: CROSPOVIDONE (12 MPA.S AT 5%); GLYCERYL MONOSTEARATE; HYDROXYPROPYL CELLULOSE (90000 WAMW); HYPROMELLOSE 2910 (5 MPA.S); MAGNESIUM STEARATE; METHACRYLIC ACID - ETHYL ACRYLATE COPOLYMER (1:1) TYPE A; MICROCRYSTALLINE CELLULOSE; POLYETHYLENE GLYCOL 4000; POLYSORBATE 80; FERRIC OXIDE RED; SILICON DIOXIDE; SODIUM HYDROXIDE; SODIUM STEARYL FUMARATE; DEXTROSE, UNSPECIFIED FORM; STARCH, CORN; SUCROSE; TALC; TITANIUM DIOXIDE; TRIETHYL CITRATE; FERRIC OXIDE YELLOW; HYDROXYPROPYL CELLULOSE (45000 WAMW); HYPROMELLOSE 2910 (6 MPA.S)

Tips for Managing Heartburn

- Do not lie flat or bend over after eating
- Do not wear tight-fitting clothing around the stomach
- Do not eat before bedtime
- Raise the head of your bed
- Avoid heartburn-causing foods such as rich, spicy, fatty or fried foods, chocolate, caffeine, alcohol and certain fruits and vegetables
- Eat slowly and avoid big meals
- If overweight, lose weight
- Quit smoking

Active ingredient (in each tablet)

Omeprazole delayed-release tablet 20 mg (equivalent to 20.6 mg omeprazole magnesium USP)

Purpose

Acid reducer

Use

- treats frequent heartburn (occurs 2 or more days a week)
- not intended for immediate relief of heartburn; this drug may take 1 to 4 days for full effect

Warnings

Allergy alert:
Do not use if you are allergic to omeprazole

Do not use if you have:

- trouble or pain swallowing food, vomiting with blood, or bloody or black stools
- heartburn with lightheadedness, sweating or dizziness
- chest pain or shoulder pain with shortness of breath; sweating; pain spreading to arms, neck or shoulders; or lightheadedness
- frequent chest pain

These may be signs of a serious condition. See your doctor.

Ask a doctor before use if you have:

- had heartburn over 3 months. This may be a sign of a more serious condition.
- frequent wheezing, particularly with heartburn
- unexplained weight loss
- nausea or vomiting
- stomach pain

Ask a doctor or pharmacist before use if you are taking:

- warfarin, clopidogrel or cilostazol (blood-thinning medicines)
- prescription antifungal or anti-yeast medicines
- diazepam (anxiety medicine)
- digoxin (heart medicine)
- tacrolimus or mycophenolate mofetil (immune system medicines)
- prescription antiretrovirals (medicines for HIV infection)
- methotrexate (arthritis medicine)

Stop use and ask a doctor if:

- your heartburn continues or worsens
- you need to take this product for more than 14 days
- you need to take more than 1 course of treatment every 4 months
- you get diarrhea
- you develop a rash or joint pain

If pregnant or breast-feeding,

ask a health professional before use.

Keep out of reach of children.

In case of overdose, get medical help or contact a Poison Control Center (1-800-222-1222) right away.

Directions

- for adults 18 years of age and older
- this product is to be used once a day (every 24 hours), every day for 14 days
- it may take 1 to 4 days for full effect; some people get complete relief of symptoms within 24 hours

14-Day Course of Treatment

- swallow 1 tablet with a glass of water before eating in the morning
- take every day for 14 days
- do not take more than 1 tablet a day
- do not use for more than 14 days unless directed by your doctor
- swallow whole. Do not chew or crush tablets.

Repeated 14-Day Courses (if needed)

- you may repeat a 14-day course every 4 months
- do not take for more than 14 days or more often than every 4 months unless directed by a doctor
- children under 18 years of age: ask a doctor. Heartburn in children may sometimes be caused by a serious condition.

Other information

- read the directions and warnings before use
- keep the carton. It contains important information.
- store at 20º to 25ºC (68º to 77º F) and protect from moisture

Inactive ingredients

crospovidone, glyceryl monostearate, hydroxypropyl cellulose, hypromellose, magnesium stearate, methacrylic acid copolymer dispersion, microcrystalline cellulose, polyethylene glycol, polysorbate 80, red iron oxide, silicified microcrystalline cellulose, sodium hydroxide, sodium stearyl fumarate, sugar spheres [which contains liquid glucose, starch (maize) and sucrose], talc, titanium dioxide, triethyl citrate and yellow iron oxide.

Questions?

Call 1-855-274-4122
Distributed by:
Fred's Inc
4300 New Getwell Road
Memphis, TN 38118
www. fredsinc.com
Questions or Comments:
1-855-331-FRED (3733)
Made in India
Code: TS/DRUGS/22/2009

PACKAGE LABEL-PRINCIPAL DISPLAY PANEL - 20 mg (14 Tablet Bottle)

fred's
Pharmacy
NDC 55315-996-74
Omeprazole
Delayed-Release Tablets 20 mg
Acid Reducer
Treats Frequent Heartburn!
24 HR
14 TABLETS
One 14-day course of treatment
May take 1 to 4 days for full effect

PACKAGE LABEL-PRINCIPAL DISPLAY PANEL - 20 mg Container Carton Label

fred's
Pharmacy
NDC 55315-996-74
Compare to active ingredient in:
Prilsec OTC®
Omeprazole
Delayed-Release Tablets 20 mg
Acid Reducer
Treats Frequent Heartburn!
24 HR
14 TABLETS
One 14-day course of treatment
May take 1 to 4 days for full effect

PACKAGE LABEL-PRINCIPAL DISPLAY PANEL - 20 mg (42 Tablet Container Carton Label)

fred's
Pharmacy
NDC 55315-996-04
Compare to active ingredient in:
Prilosec OTC®
Omeprazole
Delayed-Release Tablets 20 mg
Acid Reducer
Treats Frequent Heartburn!
24 HR
42 TABLETS
Tree 14-day course of treatment
May take 1 to 4 days for full effect